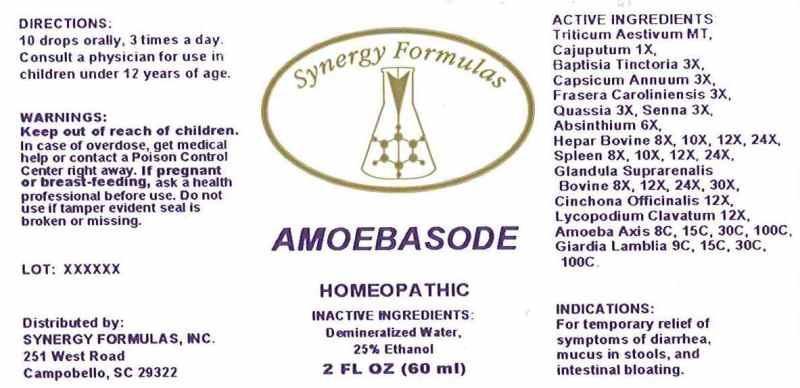 DRUG LABEL: AMOEBASODE
NDC: 43772-0047 | Form: LIQUID
Manufacturer: Synergy Formulas, Inc.
Category: homeopathic | Type: HUMAN OTC DRUG LABEL
Date: 20150123

ACTIVE INGREDIENTS: TRITICUM AESTIVUM WHOLE 1 [hp_X]/1 mL; CAJUPUT OIL 1 [hp_X]/1 mL; BAPTISIA TINCTORIA 3 [hp_X]/1 mL; CAPSICUM 3 [hp_X]/1 mL; FRASERA CAROLINIENSIS ROOT 3 [hp_X]/1 mL; QUASSIA AMARA WOOD 3 [hp_X]/1 mL; SENNA LEAF 3 [hp_X]/1 mL; WORMWOOD 6 [hp_X]/1 mL; BEEF LIVER 8 [hp_X]/1 mL; BOS TAURUS SPLEEN 8 [hp_X]/1 mL; BOS TAURUS ADRENAL GLAND 8 [hp_X]/1 mL; CINCHONA OFFICINALIS BARK 12 [hp_X]/1 mL; LYCOPODIUM CLAVATUM SPORE 12 [hp_X]/1 mL; AMOEBA PROTEUS 8 [hp_C]/1 mL; GIARDIA LAMBLIA 9 [hp_C]/1 mL
INACTIVE INGREDIENTS: WATER; ALCOHOL

DRUG FACTS:

ACTIVE INGREDIENTS:

TRITICUM AESTIVUM MT, CAJUPUTUM 1X, BAPTISIA TINCTORIA 3X, CAPSICUM ANNUUM 3X, FRASERA CAROLINIENSIS 3X, QUASSIA (AMARA) 3X, SENNA (CASSIA ANGUSTIFOLIA) 3X, ABSINTHIUM 6X, HEPAR BOVINE 8X, 10X, 12X, 24X, SPLEEN (BOVINE) 8X, 10X, 12X, 24X, GLANDULA SUPRARENALIS BOVINE 8X, 12X, 24X, 30X, CINCHONA OFFICINALIS 12X, LYCOPODIUM CLAVATUM 12X, AMOEBA AXIS 8C, 15C, 30C, 100C, GIARDIA LAMBLIA 9C, 15C, 30C, 100C.

INDICATIONS:

For temporary relief of symptoms of diarrhea, mucus in stools, and intestinal bloating.

WARNINGS:

Keep out of reach of children. In case of overdose, get medical help or contact a Poison Control Center right away.

If pregnant or breast-feeding, ask a health professional before use.

Do not use if tamper evident seal is broken or missing.

Keep out of reach of children. In case of overdose, get medial help or contact a Poison Control Center right away.

DIRECTIONS:

10 drops orally, 3 times a day. Consult a physician for use in children under 12 years of age.

INDICATIONS:

For temporary relief of symptoms of diarrhea, mucus in stools, and intestinal bloating.

INACTIVE INGREDIENTS:

Demineralized Water, 25% Ethanol

QUESTIONS:

Distributed by:

SYNERGY FORMULAS, INC.

251 West Road

Campobello, SC 29322

PACKAGE DISPLAY LABEL:

Synergy Formula

AMOEBASODE

HOMEOPATHIC

2 FL OZ (60 mL)